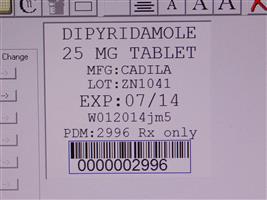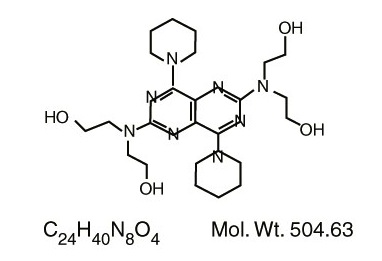 DRUG LABEL: Dipyridamole
NDC: 68151-2996 | Form: TABLET
Manufacturer: Carilion Materials Management
Category: prescription | Type: HUMAN PRESCRIPTION DRUG LABEL
Date: 20120215

ACTIVE INGREDIENTS: DIPYRIDAMOLE 25 mg/1 1
INACTIVE INGREDIENTS: ACACIA; CARNAUBA WAX; STARCH, CORN; LACTOSE MONOHYDRATE; MAGNESIUM STEARATE; D&C YELLOW NO. 10; D&C RED NO. 30; ALUMINUM OXIDE; SODIUM BENZOATE; METHYLPARABEN; PROPYLPARABEN; POLYETHYLENE GLYCOLS; POVIDONES; SUCROSE; TALC; TITANIUM DIOXIDE; WHITE WAX

DIPYRIDAMOLE Tablets USP

DESCRIPTION

Dipyridamole Tablets USP are a platelet inhibitor chemically described as 2,2',2'',2'''-[(4,8-Dipiperidinopyrimido[5,4- ]pyrimidine-2,6-diyl)dinitrilo]-tetraethanol. It has the following structural formula: d

Dipyridamole is an odorless yellow crystalline powder, having a bitter taste. It is soluble in dilute acids, methanol and chloroform, and practically insoluble in water.

Dipyridamole Tablets USP for oral administration contain:

dipyridamole USP 25 mg, 50 mg and 75 mg, respectively. Active Ingredient TABLETS 25 mg, 50 mg, and 75 mg:

acacia, carnauba wax, corn starch, edible white ink, lactose monohydrate, magnesium stearate, D&C yellow #10 aluminum lake, D&C red #30, helendon aluminum pink lake, sodium benzoate, methylparaben, propylparaben, polyethylene glycol, povidone, sucrose, talc, titanium dioxide, and white wax. Inactive Ingredients TABLETS 25 mg, 50 mg, and 75 mg:

CLINICAL PHARMACOLOGY

It is believed that platelet reactivity and interaction with prosthetic cardiac valve surfaces, resulting in abnormally shortened platelet survival time, is a significant factor in thromboembolic complications occurring in connection with prosthetic heart valve replacement.

Dipyridamole tablets have been found to lengthen abnormally shortened platelet survival time in a dose-dependent manner.

In three randomized controlled clinical trials involving 854 patients who had undergone surgical placement of a prosthetic heart valve, dipyridamole tablets, in combination with warfarin, decreased the incidence of postoperative thromboembolic events by 62 to 91% compared to warfarin treatment alone. The incidence of thromboembolic events in patients receiving the combination of dipyridamole tablets and warfarin ranged from 1.2 to 1.8%. In three additional studies involving 392 patients taking dipyridamole tablets and coumarin-like anticoagulants, the incidence of thromboembolic events ranged from 2.3 to 6.9%.

In these trials, the coumarin anticoagulant was begun between 24 hours and 4 days postoperatively, and the dipyridamole tablets USP were begun between 24 hours and 10 days postoperatively. The length of follow-up in these trials varied from 1 to 2 years.

Dipyridamole tablets do not influence prothrombin time or activity measurements when administered with warfarin.

Mechanism of Action

Dipyridamole inhibits the uptake of adenosine into platelets, endothelial cells and erythrocytes and ; the inhibition occurs in a dose-dependent manner at therapeutic concentrations (0.5-1.9 μg/mL). This inhibition results in an increase in local concentrations of adenosine which acts on the platelet A2-receptor thereby stimulating platelet adenylate cyclase and increasing platelet cyclic-3',5'-adenosine monophosphate (cAMP) levels. Via this mechanism, platelet aggregation is inhibited in response to various stimuli such as platelet activating factor (PAF), collagen and adenosine diphosphate (ADP). in vitroin vivo

Dipyridamole inhibits phosphodiesterase (PDE) in various tissues. While the inhibition of cAMPPDE is weak, therapeutic levels of dipyridamole inhibit cyclic-3',5'-guanosine monophosphate-PDE (cGMP-PDE), thereby augmenting the increase in cGMP produced by EDRF (endothelium-derived relaxing factor, now identified as nitric oxide).

Hemodynamics

In dogs intraduodenal doses of dipyridamole of 0.5 to 4.0 mg/kg produced dose-related decreases in systemic and coronary vascular resistance leading to decreases in systemic blood pressure and increases in coronary blood flow. Onset of action was in about 24 minutes and effects persisted for about 3 hours.

Similar effects were observed following IV dipyridamole in doses ranging from 0.025 to 2.0 mg/kg.

In man the same qualitative hemodynamic effects have been observed. However, acute intravenous administration of dipyridamole may worsen regional myocardial perfusion distal to partial occlusion of coronary arteries.

Pharmacokinetics and Metabolism

Following an oral dose of dipyridamole tablets, the average time to peak concentration is about 75 minutes. The decline in plasma concentration following a dose of dipyridamole tablets fits a two-compartment model. The alpha half-life (the initial decline following peak concentration) is approximately 40 minutes. The beta half-life (the terminal decline in plasma concentration) is approximately 10 hours. Dipyridamole is highly bound to plasma proteins. It is metabolized in the liver where it is conjugated as a glucuronide and excreted with the bile.

INDICATIONS AND USAGE

Dipyridamole Tablets USP are indicated as an adjunct to coumarin anticoagulants in the prevention of postoperative thromboembolic complications of cardiac valve replacement.

CONTRAINDICATIONS

Hypersensitivity to dipyridamole and any of the other components.

PRECAUTIONS

General

Dipyridamole has a vasodilatory effect and should be used with caution in patients with severe coronary artery disease (e.g., unstable angina or recently sustained myocardial infarction). Chest pain may be aggravated in patients with underlying coronary artery disease who are receiving dipyridamole. Coronary Artery Disease:

Elevations of hepatic enzymes and hepatic failure have been reported in association with dipyridamole administration. Hepatic Insufficiency:

Dipyridamole should be used with caution in patients with hypotension since it can produce peripheral vasodilation. Hypotension:

Laboratory Tests

Dipyridamole has been associated with elevated hepatic enzymes.

Drug Interactions

No pharmacokinetic drug-drug interaction studies were conducted with dipyridamole tablets USP. The following information was obtained from the literature.

Dipyridamole has been reported to increase the plasma levels and cardiovascular effects of adenosine. Adjustment of adenosine dosage may be necessary. Adenosine:

Dipyridamole may counteract the anticholinesterase effect of cholinesterase inhibitors, thereby potentially aggravating myasthenia gravis. Cholinesterase Inhibitors:

Carcinogenesis, Mutagenesis, Impairment of Fertility

In studies in which dipyridamole was administered in the feed to mice (up to 111 weeks in males and females) and rats (up to 128 weeks in males and up to 142 weeks in females), there was no evidence of drug-related carcinogenesis.

The highest dose administered in these studies (75 mg/kg/day) was, on a mg/m basis, about equivalent to the maximum recommended daily human oral dose (MRHD) in mice and about twice the MRHD in rats. Mutagenicity tests of dipyridamole with bacterial and mammalian cell systems were negative. There was no evidence of impaired fertility when dipyridamole was administered to male and female rats at oral doses up to 500 mg/kg/day (about 12 times the MRHD on a mg/m basis). A significant reduction in number of corpora lutea with consequent reduction in implantations and live fetuses was, however, observed at 1250 mg/kg (more than 30 times the MRHD on a mg/m basis).^2^2^2

Pregnancy

Teratogenic Effect

Reproduction studies have been performed in mice, rabbits and rats at oral dipyridamole doses of up to 125 mg/kg, 40 mg/kg and 1000 mg/kg, respectively (about 11⁄2, 2 and 25 times the maximum recommended daily human oral dose, respectively, on a mg/m basis) and have revealed no evidence of harm to the fetus due to dipyridamole. There are, however, no adequate and well controlled studies in pregnant women. Because animal reproduction studies are not always predictive of human response, dipyridamole tablets should be used during pregnancy only if clearly needed. Pregnancy Category B.^2

Nursing Mothers

As dipyridamole is excreted in human milk, caution should be exercised when dipyridamole tablets are administered to a nursing woman.

Pediatric Use

Safety and effectiveness in the pediatric population below the age of 12 years have not been established.

ADVERSE REACTIONS

Adverse reactions at therapeutic doses are usually minimal and transient. On long-term use of dipyridamole tablets initial side effects usually disappear. The following reactions in Table 1 were reported in two heart valve replacement trials comparing dipyridamole tablets and war- farin therapy to either warfarin alone or warfarin and placebo:

Table 1 Adverse Reactions Reported in 2 Heart Valve Replacement Trials
Adverse Reaction | Dipyridamole Tablets/Warfarin | Placebo/Warfarin
Number of Patients | 147 | 170
Dizziness | 13.6% | 8.2%
Abdominal distress | 6.1% | 3.5%
Headache | 2.3% | 0.0%
Rash | 2.3% | 1.1%

Other reactions from uncontrolled studies include diarrhea, vomiting, flushing and pruritus. In addition, angina pectoris has been reported rarely and there have been rare reports of liver dysfunction. On those uncommon occasions when adverse reactions have been persistent or intolerable, they have ceased on withdrawal of the medication.

When dipyridamole tablets USP were administered concomitantly with warfarin, bleeding was no greater in frequency or severity than that observed when warfarin was administered alone. In rare cases, increased bleeding during or after surgery has been observed.

In post-marketing reporting experience, there have been rare reports of hypersensitivity reac- tions (such as rash, urticaria, severe bronchospasm, and angioedema), larynx edema, fatigue, malaise, myalgia, arthritis, nausea, dyspepsia, paresthesia, hepatitis, thrombocytopenia, alo- pecia, cholelithiasis, hypotension, palpitation, and tachycardia.

OVERDOSAGE

In case of real or suspected overdose, seek medical attention or contact a Poison Control Center immediately. Careful medical management is essential. Based upon the known hemodynamic effects of dipyridamole, symptoms such as warm feeling, flushes, sweating, restlessness, feeling of weakness and dizziness may occur. A drop in blood pressure and tachycardia might also be observed.

Symptomatic treatment is recommended, possibly including a vasopressor drug. Gastric lavage should be considered. Administration of xanthine derivatives (e.g., aminophylline) may reverse the hemodynamic effects of dipyridamole overdose. Since dipyridamole is highly protein bound, dialysis is not likely to be of benefit.

DOSAGE AND ADMINISTRATION

The recommended dose is 75-100 mg four times daily as an adjunct to the usual warfarin therapy. Please note that aspirin is not to be administered concomitantly with coumarin anticoagulants. Adjunctive Use in Prophylaxis of Thromboembolism after Cardiac Valve Replacement.

HOW SUPPLIED

NDC:68151-2996-0 in a PACKAGE of 1 TABLETS